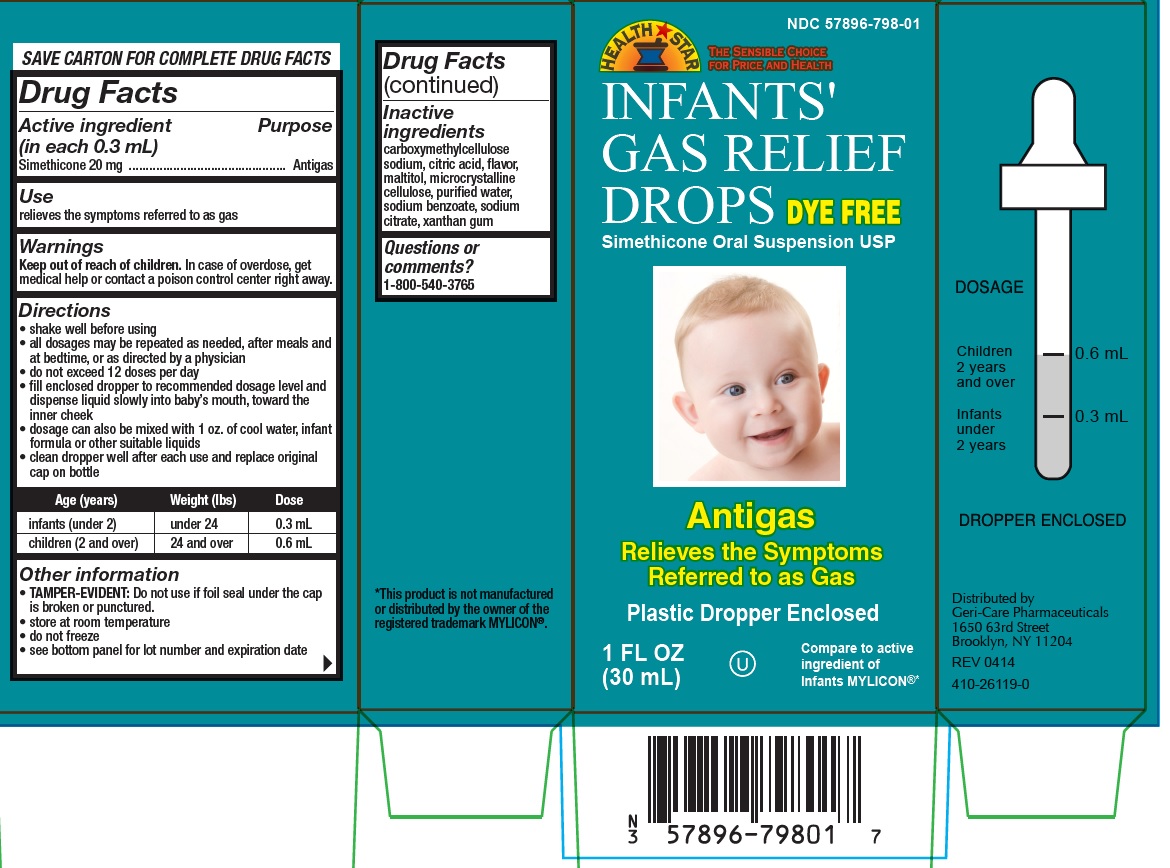 DRUG LABEL: INFANTS GAS RELIEF
NDC: 57896-798 | Form: SUSPENSION
Manufacturer: Geri-Care Pharmaceuticals, Corp
Category: otc | Type: HUMAN OTC DRUG LABEL
Date: 20231101

ACTIVE INGREDIENTS: DIMETHICONE 20 mg/0.3 mL
INACTIVE INGREDIENTS: ANHYDROUS CITRIC ACID; CARBOXYMETHYLCELLULOSE SODIUM; MALTITOL; CELLULOSE, MICROCRYSTALLINE; WATER; SODIUM BENZOATE; SODIUM CITRATE; XANTHAN GUM

hst infants gas relief

Active ingredient (in each 0.3 mL)

Simethicone 20 mg

Purpose

Antigas

Use

relieves the symptoms referred to as gas

Warnings

Keep out of reach of children. In case of overdose, get medical help or contact a poison control center right away.

Directions

- shake well before using
- all dosages may be repeated as needed, after meals and at bedtime, or as directed by a physician
- do not exceed 12 doses per day
- fill enclosed dropper to recommended dosage level anddispense liquid slowly into baby’s mouth, toward the inner cheek dosage can also be mixed with 1 oz. of cool water, infant formula or other suitable liquids
- clean dropper well after each use and replace original cap on bottle

Age (years) | Weight (lbs) | Dose
infants (under 2) | under 24 | 0.3 mL
children (2 and over) | 24 and over | 0.6 mL

Other information

- TAMPER-EVIDENT: Do not use if foil seal under the cap is broken or punctured.
- store at room temperature
- do not freeze
- see bottom panel for lot number and expiration date

Inactive ingredients

carboxymethylcellulose sodium, citric acid, flavor, maltitol, microcrystalline cellulose, purified water, sodium benzoate, sodium citrate, xanthan gum

Questions or comments?

1-800-540-3765

Package Label

NDC 57896-798-01

Health star

the sensible choice for price and health

INFANTS'
GAS RELIEF
DROPS

dye free

Simethicone Oral Suspension USP

Antigas
Relieves the Symptoms
Referred to as Gas

Plastic Dropper Enclosed
Antigas
Relieves the Symptoms
Referred to as Gas
Simethicone Oral Suspension USP
1 FL OZ
(30 mL)
Compare to active
ingredient of
Infants MYLICON®*